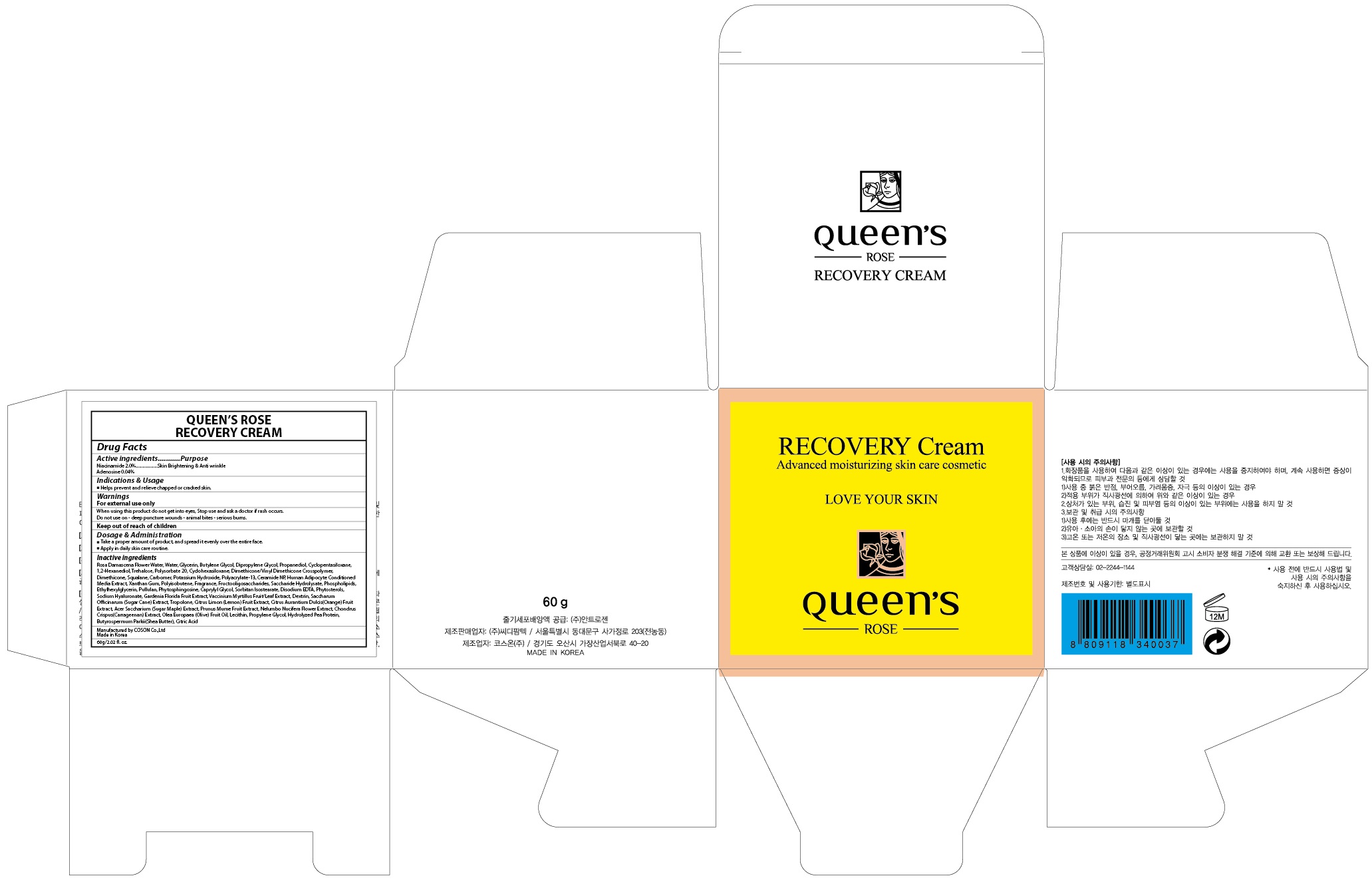 DRUG LABEL: QUEENS ROSE RECOVERY
NDC: 71252-050 | Form: CREAM
Manufacturer: Cdpharmtec Co.,ltd
Category: otc | Type: HUMAN OTC DRUG LABEL
Date: 20170324

ACTIVE INGREDIENTS: Niacinamide 1.2 g/60 g; Adenosine 0.024 g/60 g
INACTIVE INGREDIENTS: ROSA DAMASCENA FLOWER OIL; Water

ACTIVE INGREDIENT

Active ingredients: Niacinamide 2.0%, Adenosine 0.04%

INACTIVE INGREDIENT

Inactive ingredients: Rosa Damascena Flower Water, Water, Glycerin, Butylene Glycol, Dipropylene Glycol, Propanediol, Cyclopentasiloxane, 1,2-Hexanediol, Trehalose, Polysorbate 20, Cyclohexasiloxane, Dimethicone/Vinyl Dimethicone Crosspolymer, Dimethicone, Squalane, Carbomer, Potassium Hydroxide, Polyacrylate-13, Ceramide NP, Human Adipocyte Conditioned Media Extract, Xanthan Gum, Polyisobutene, Fragrance, Fructooligosaccharides, Saccharide Hydrolysate, Phospholipids, Ethylhexylglycerin, Pullulan, Phytosphingosine, Caprylyl Glycol, Sorbitan Isostearate, Disodium EDTA, Phytosterols, Sodium Hyaluronate, Gardenia Florida Fruit Extract, Vaccinium Myrtillus Fruit/Leaf Extract, Dextrin, Saccharum Officinarum (Sugar Cane) Extract, Tropolone, Citrus Limon (Lemon) Fruit Extract, Citrus Aurantium Dulcis(Orange) Fruit Extract, Acer Saccharium (Sugar Maple) Extract, Prunus Mume Fruit Extract, Nelumbo Nucifera Flower Extract, Chondrus Crispus(Carrageenan) Extract, Olea Europaea (Olive) Fruit Oil, Lecithin, Propylene Glycol, Hydrolyzed Pea Protein, Butyrospermum Parkii(Shea Butter), Citric Acid

PURPOSE

Purpose: Skin Brightening & Anti wrinkle

WARNINGS

Warnings: For external use only When using this product do not get into eyes, Stop use and ask a doctor if rash occurs. Do not use on - deep puncture wounds - animal bites - serious burns.

KEEP OUT OF REACH OF CHILDREN

INDICATIONS & USAGE

Indications & Usage: Helps prevent and relieve chapped or cracked skin.

DOSAGE & ADMINISTRATION

Dosage & Administration: - Take a proper amount of product, and spread it evenly over the entire face. - Apply in daily skin care routine.